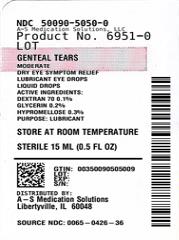 DRUG LABEL: GENTEAL TEARS
NDC: 50090-5050 | Form: SOLUTION/ DROPS
Manufacturer: A-S Medication Solutions
Category: otc | Type: HUMAN OTC DRUG LABEL
Date: 20240121

ACTIVE INGREDIENTS: DEXTRAN 70 1 mg/1 mL; GLYCERIN 2 mg/1 mL; HYPROMELLOSES 3 mg/1 mL
INACTIVE INGREDIENTS: Boric Acid; Calcium Chloride; Glycine; Hydrochloric Acid; Sodium Hydroxide; Magnesium Chloride; Polidronium Chloride; Polysorbate 80; Potassium Chloride; Water; Sodium Chloride; Zinc Chloride

GENTEAL TEARS

ACTIVE INGREDIENT

Active ingredients | Purpose
Dextran 70 0.1% | Lubricant
Glycerin 0.2% | Lubricant
Hypromellose 0.3% | Lubricant

Uses

- temporary relief of burning and irritation due to dryness of the eye
- as a protectant against further irritation
- temporary relief of discomfort due to minor irritations of the eye or to exposure to wind or sun

Warnings

For external use only

Do not use

- if this solution changes color or becomes cloudy
- if you are sensitive to any ingredient in this product

When using this product

- do not touch tip of container to any surface to avoid contamination
- replace cap after each use

Stop use and ask a doctor if you experience any of the following:

- you feel eye pain
- changes in vision
- continued redness or irritation of the eye
- condition worsens or persists for more than 72 hours

Keep out of reach of children.

If swallowed, get medical help or contact a Poison Control Center right away.

Directions

- put 1 or 2 drops in the affected eye(s) as needed

Other Information

- store at room temperature

Inactive ingredients:

boric acid, calcium chloride, glycine, hydrochloric acid and/or sodium hydroxide (to adjust pH), magnesium chloride, POLYQUAD* (polyquaternium-1) 0.001% preservative, polysorbate 80, potassium chloride, purified water, sodium chloride, zinc chloride.

HOW SUPPLIED

Product: 50090-5050

NDC: 50090-5050-0 15 mL in a BOTTLE, DROPPER / 1 in a CARTON

Questions?

In the U.S. call 1-800-757-9195
(Mon-Fri 9AM-5PM CST)
alcon.medinfo@alcon.com